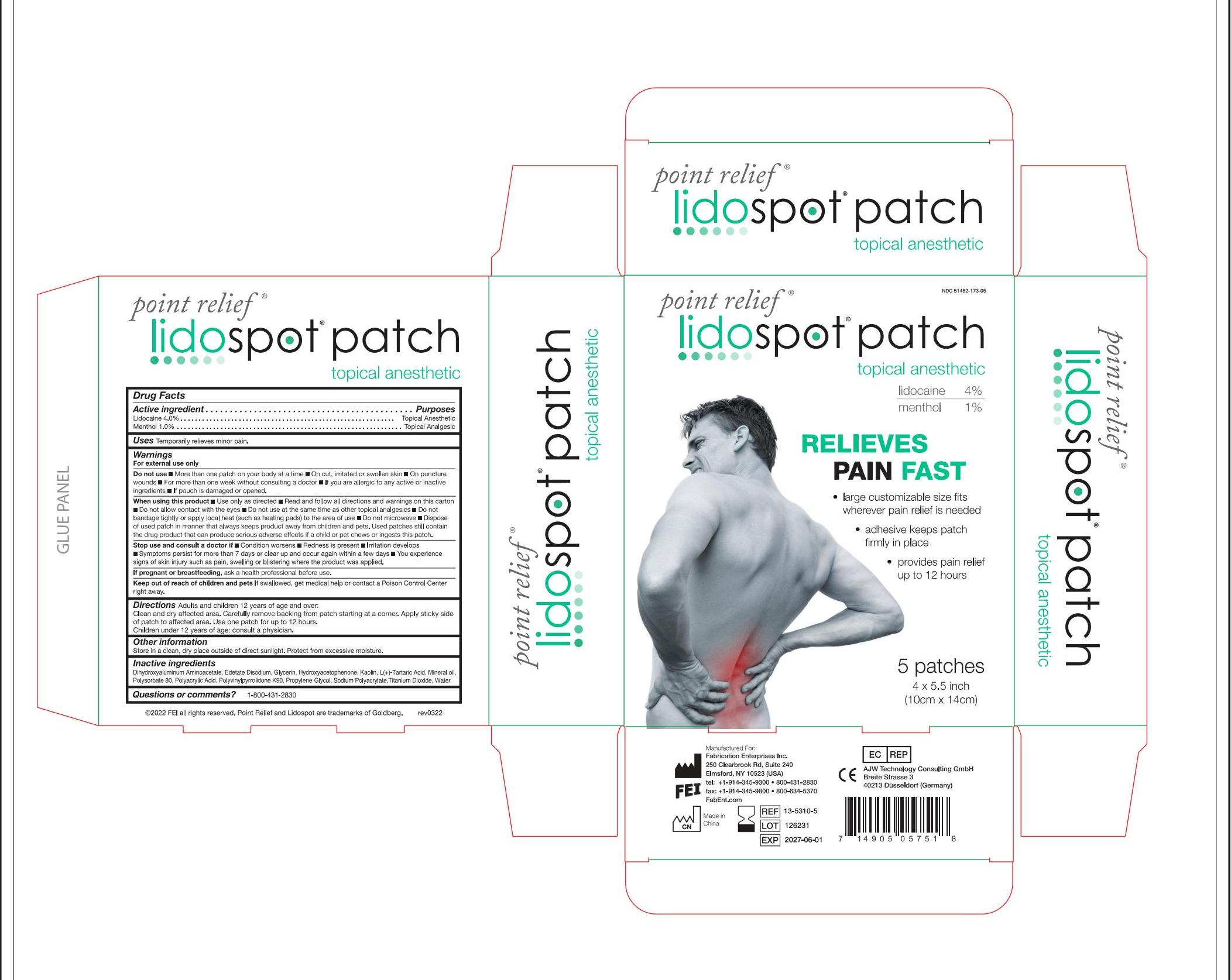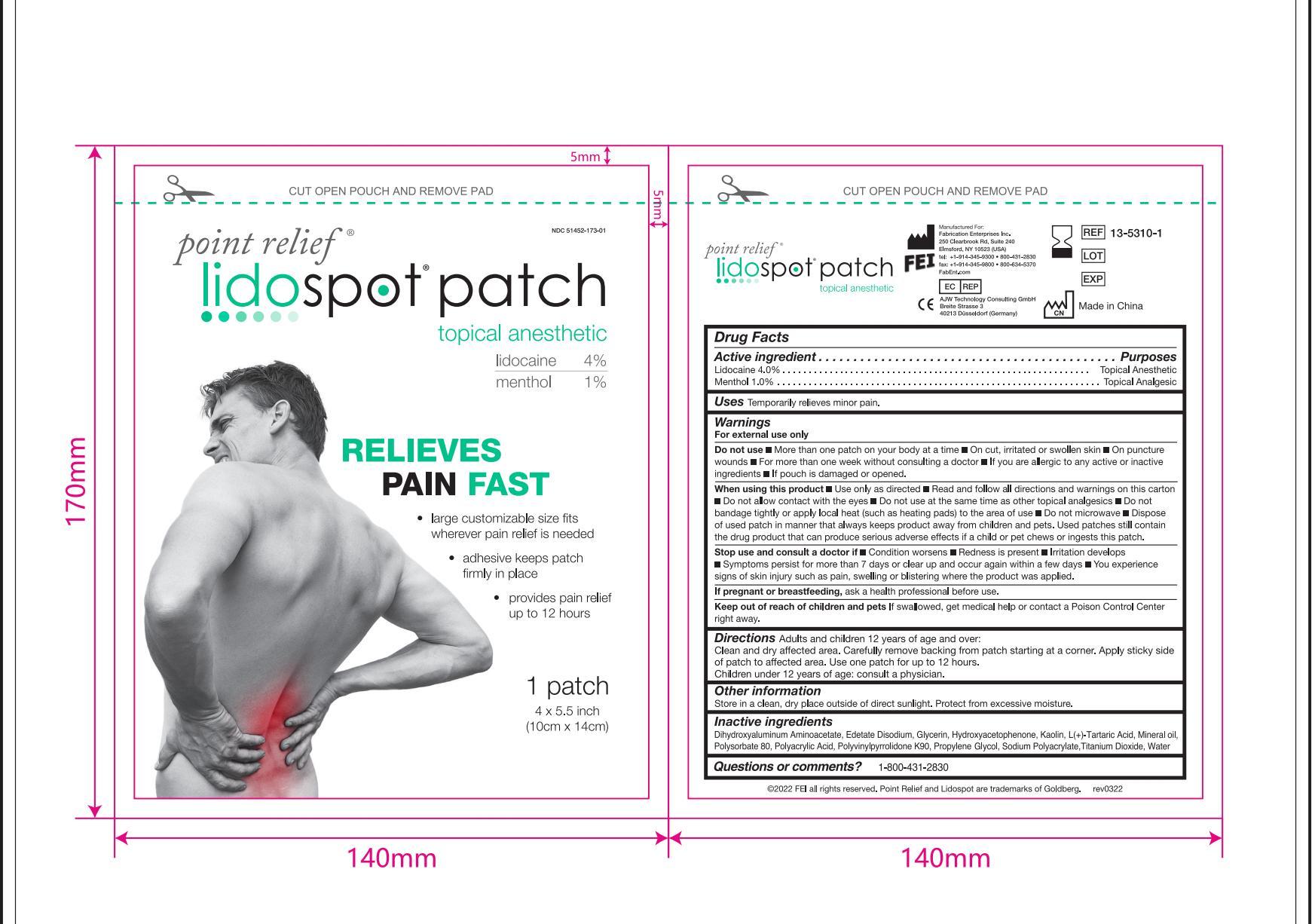 DRUG LABEL: Lidospot patch
NDC: 51452-172 | Form: PATCH
Manufacturer: Fabrication Enterprises Inc 
Category: otc | Type: HUMAN OTC DRUG LABEL
Date: 20251212

ACTIVE INGREDIENTS: MENTHOL 0.01 g/1 g; LIDOCAINE 0.04 g/1 g
INACTIVE INGREDIENTS: KAOLIN; TARTARIC ACID; WATER; DIHYDROXYALUMINUM AMINOACETATE ANHYDROUS; PROPYLENE GLYCOL; POLYACRYLIC ACID (250000 MW); SODIUM POLYACRYLATE (2500000 MW); TITANIUM DIOXIDE; MINERAL OIL; POLYSORBATE 80; GLYCERIN; EDETATE DISODIUM; POVIDONE K90; HYDROXYACETOPHENONE

51452-172；Zeey, LIDOCAINE&MENTHOL PAIN RELIEF GEL-PATCH, N 5, N 10, N 15

Active Ingredient

Lidocaine 4% w/w ...... Purpose: Topical anesthetic

Menthol 1% w/w ...... Purpose: Topical analgesic

Purposes

Topical anesthetic (Lidocaine)

Topical analgesic (Menthol)

Uses

Temporarily relieves minor pain.

Warnings

For external use only

When using this product:

- Use only as directed
- Read and follow all directions and warnings on this carton
- Do not alow contact with the eyes
- Do not use at the same time as other topical analgesics
- Do not bandage tightly or apply local heat (such as heating pads) to the area of use
- Do not microwave
- Dispose of used patch in manner that always keeps product away from children and pets. Used patches stil containthe drug product that can produce serious adverse effects if a child or pet chews or ingests this patch.

Do not use:

- More than 1 patch on your body at a time
- On cut, irritated or swollen skin
- On puncture wounds
- For more than one week without consulting a doctor
- lf you are allergic to any active or inactive ingredients
- lf pouch is damaged or opened.

Stop use and ask a doctor if:

Condition worsens

Redness is present

lrritation develops

Symptoms persist for more than 7 days or clear up and occur again within a few days

You experiencesigns of skin injury such as pain, swelling or blistering where the product was applied.

If pregnant or breast-feeding,

Ask a health professional before use

Keep out of reach of children.

If swallowed, get medical help or contact a Poison Control Center right away

Directions

Adult and Children 12 years of age and over:

- Clean and dry affected area Carefully remove backing from patch starting at a corner. Apply sticky side of patch to affected area. Use one patch for up to 12 hours.

Children under 12 years of age:consult a physician.

Inactive Ingredients

Dihydroxyaluminium Aminoacetate, Edetate Disodium, Glycerin, Hydroxyacetophenone, Kaolin,L(+)-Tartaric Acid,Mineral oil,Polysorbate 80, Polyacrylic Acid, Polyvinylpyrrolidone K90, Propylene Glycol, Sodium Polyacrylate, Titanium Dioxide,Water,

Questions or Comments

1-800-431-2830

Other information

- Store in a clean, dry place outside of direct sunlight, Protect from excessive moisture.